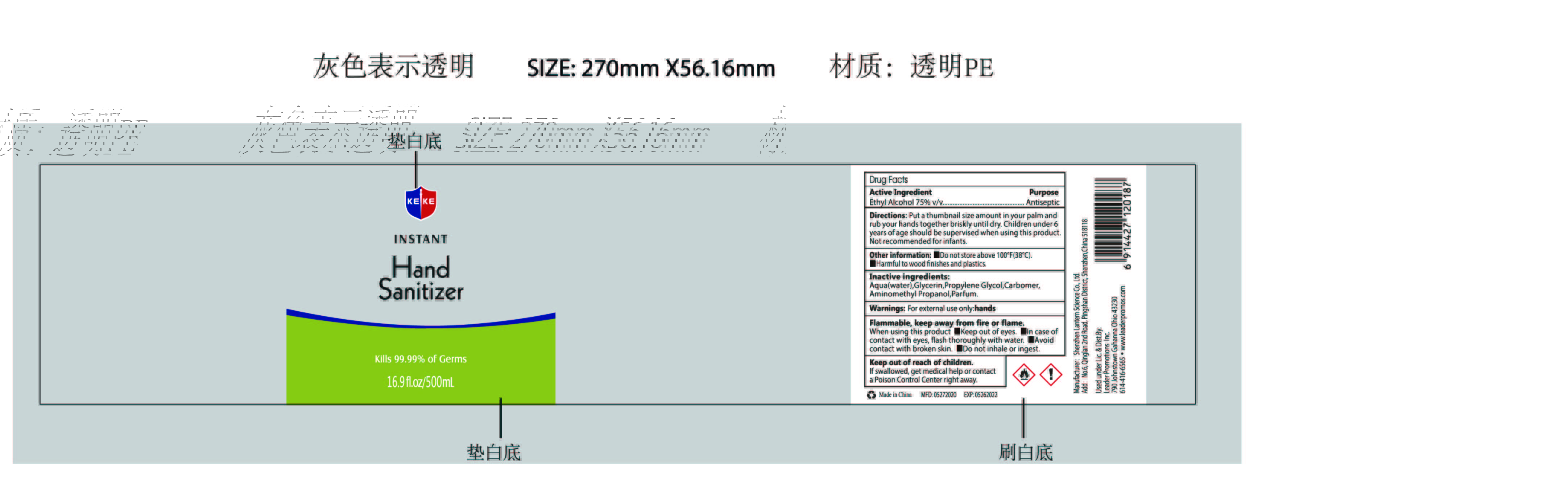 DRUG LABEL: KEKE Hand sanitizer 500ml
NDC: 54860-293 | Form: LIQUID
Manufacturer: Shenzhen Lantern Science Co.,Ltd.
Category: otc | Type: HUMAN OTC DRUG LABEL
Date: 20200709

ACTIVE INGREDIENTS: ALCOHOL 75 mL/100 mL
INACTIVE INGREDIENTS: CARBOMER 940 0.35 mL/100 mL; WATER 24.42 mL/100 mL; AMINOMETHYLPROPANOL 0.11 mL/100 mL; GLYCERIN 0.01 mL/100 mL; PROPYLENE GLYCOL 0.01 mL/100 mL; LEMON 0.1 mL/100 mL

KEKE Hand sanitizer 500ml

Active Ingredient

Active Ingredients Purpose

Ethyl Alcohol 75% Antiseptic

Warning

For external use only:hands

flammable,keep away from heat and flame.

WARNINGS AND PRECAUTIONS

For external use only.

Flammable, keep away from heat and flame.

STOP USE

Discontinue if skin becomes irritated and ask a doctor .

Keep out of reach of children. In case of accidental ingestion, seek professional assistance or contact a poson control center immediately.

Inactive ingredients

Aqua(water),Glycerin,Propylene Glycol,Carbomer,Aminomethyl Propanol,Parfum.

Directions

Put a thumbnail size amount in your palm and rub your hands together briskly until dry.CHildren under 6 years of age should be supervised when using this product.Not recommended for infants.

When using this product

keep out of eyes. In case of contact with eyes, flush thoroughly with water.

Do not inhale or ingest.

Avoid contact with broken skin.

Other information

Do not store above 105F.

May discolor some fabrics.

Harmful to wood finishes and plastics.

OTHER SAFETY INFORMATION

Do not store above100℉（38℃）

Harmful to wood finishes and plastics.

When using this product

Keep out of eyes,In case of contact with eyes,flush thoroughly with water.

Avoid contact with broken skin.

Do not inhale of ingest.

Keep out of reach of children

If swallowed,get medical help or contact a Poison Control Center right away.

dosage

Put a thumbnail size amount in your palm

Purpose

Antiseptic